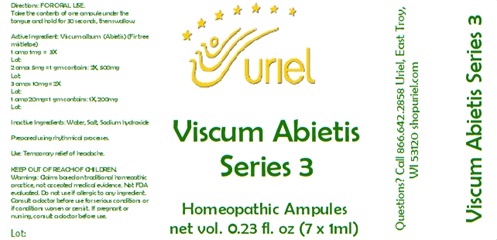 DRUG LABEL: Viscum Abietis Series 3 7ml
NDC: 48951-9265 | Form: LIQUID
Manufacturer: Uriel Pharmacy Inc.
Category: homeopathic | Type: HUMAN OTC DRUG LABEL
Date: 20241204

ACTIVE INGREDIENTS: VISCUM ALBUM FRUITING TOP 1 [hp_X]/1 mL
INACTIVE INGREDIENTS: WATER; SODIUM CHLORIDE; SODIUM HYDROXIDE

Viscum Abietis Series 3 7ml

INDICATIONS AND USAGE

Directions: FOR ORAL USE.

DOSAGE AND ADMINISTRATION

Take the contents of one ampule
under the tongue and hold for
30 seconds, then swallow.

Active Ingredient: Viscum Abietis (Fir tree mistletoe) 1 amp 1mg = 3X, 2 amps 5mg = 1 gm contains: 2X, 500mg,
3 amps 10mg = 2X,1 amp 20mg= 1 gm contains: 1X, 200mg

PURPOSE

Use: Temporary relief of headache.

Inactive Ingredients: Water, Salt, Sodium Hydroxide

Prepared using rhythmical processes.

KEEP OUT OF REACH OF CHILDREN.

WARNINGS

Warnings: Claims based on traditional homepathic practice, not accepted medical evidence. Not FDA evaluated. Do not use if allergic to any ingredient. Consult a doctor before use for serious conditions or if conditions worsen or persist. If pregnant or nursing, consult a doctor before use.

QUESTIONS

Questions? Call 866.642.2858 Uriel, East Troy, WI 53120 shopuriel.com Lot: